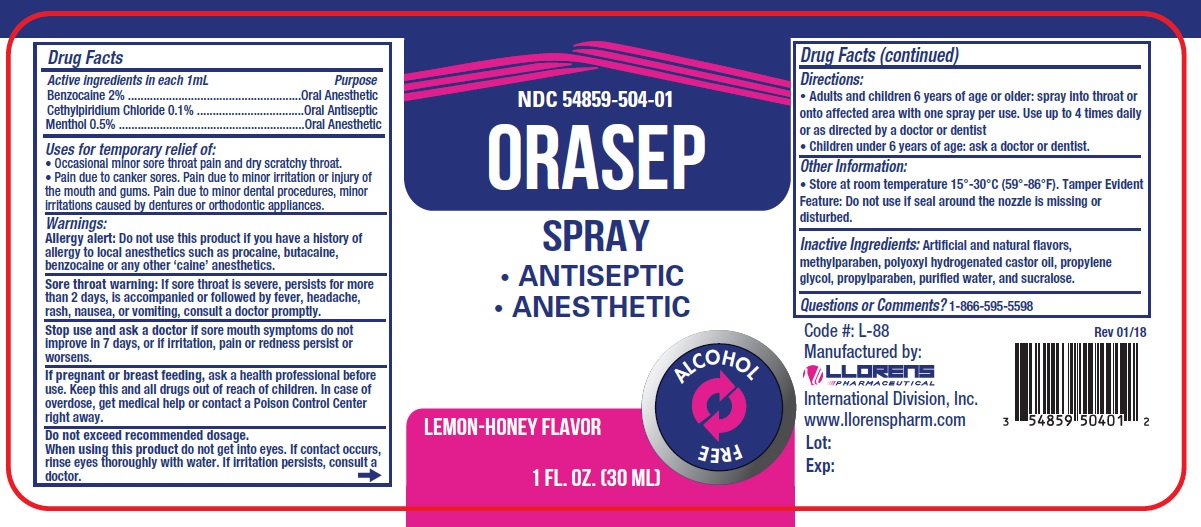 DRUG LABEL: Orasep
NDC: 54859-504 | Form: LIQUID
Manufacturer: Llorens Pharmaceutical International Division
Category: otc | Type: HUMAN OTC DRUG LABEL
Date: 20251231

ACTIVE INGREDIENTS: BENZOCAINE 2 mg/100 mL; MENTHOL 0.5 mg/100 mL; CETYLPYRIDINIUM CHLORIDE 0.1 mg/100 mL
INACTIVE INGREDIENTS: CASTOR OIL; METHYLPARABEN; PROPYLENE GLYCOL; PROPYLPARABEN; WATER; SUCRALOSE

Llorens- Orasep Spray 504

Active Ingredients:

Benzocaine...................... 2% Anesthetic

Cetylpyridinium Chloride..........0.1% Antiseptic

Menthol.................................0.5% Anesthetic

Purpose

Oral anesthetic

Oral antiseptic

INDICATIONS AND USAGE

Uses for temporary relief of:

- Occasional minor sore throat pain and dry scratch throat.
- Pain due to canker sores. Pain due to minor irritation or injury of the mouth and gums. Pain due to minor dental procedures, minor irritations cause by dentures or orthodontic appliances.

Warnings:

Allergy alert: Do not use this product if you have a history of allergy to local anesthetics such as procaine, butacaine, benzocaine or any other 'caine' anesthetics.

Sore throat warning: If sore throat is sever, persists for more than2 days, is accompanied or followed by fever, headache, rash, nausea, or vomitings, consult a doctor promptly.

Stop use and ask a doctor if sore mouth symptoms do not improve in 7 days, or if irritation, pain or redness persist or worsens.

Do not exceed recommended dosage.

When using this product do not get into eyes. If contact occurs, rinse eyes thoroughly with water. If irritation persists, consult a doctor.

KEEP OUT OF REACH OF CHILDREN

Keep this and all drugs out of the reach of children.In case of overdose, get medical help or contact a Poison Control Center right away.

PREGNANCY OR BREAST FEEDING

If pregnant or breast feeding,ask a health professional before use.

Directions:

- Adults and children 6 years of age or older: spray into throat or onto affected area with one spray per use. Use up to 4 times daily or as directed by a doctor or dentist
- Children under 6 years of age: ask a doctor or dentist.

INACTIVE INGREDIENT

Inactive Ingredients: Artificial and natural flavors, methylparaben, polyoxyl hydrogenated castor oil, propylene glycol, propylparaben, purified water, and sucralose.

Questions or comments? 1-866-595-5598